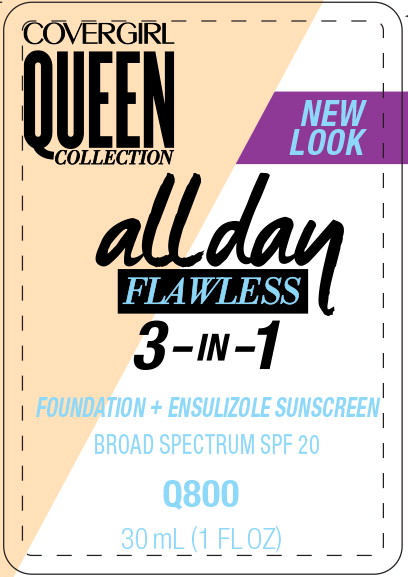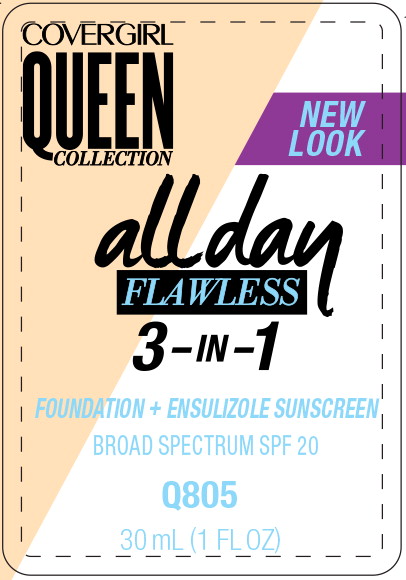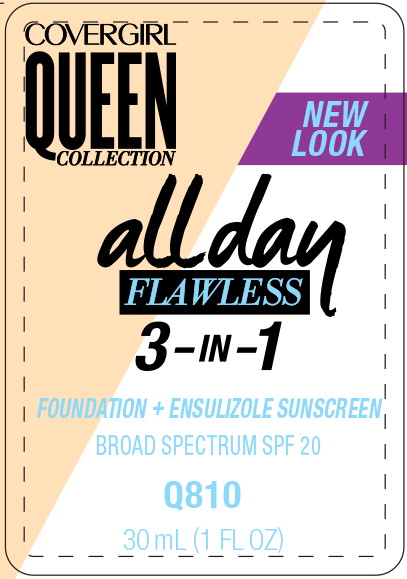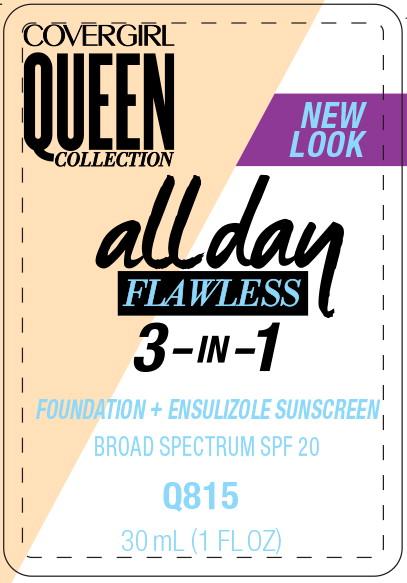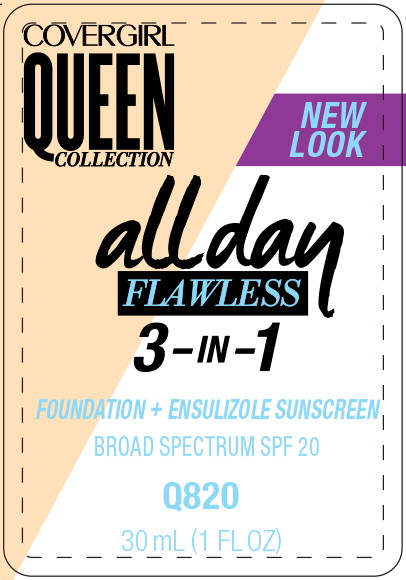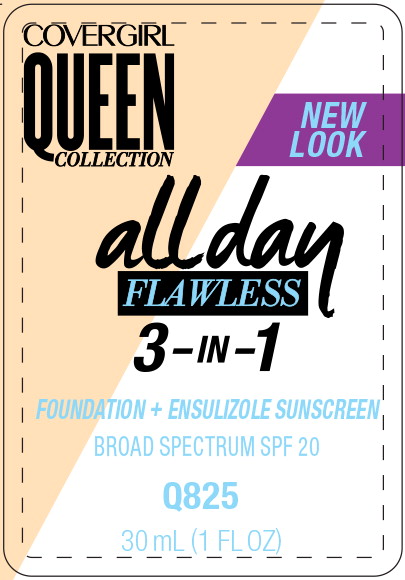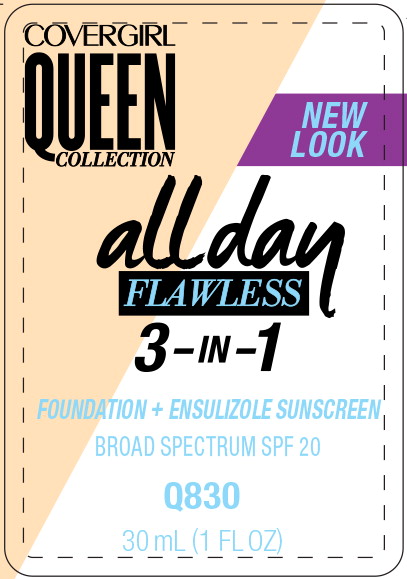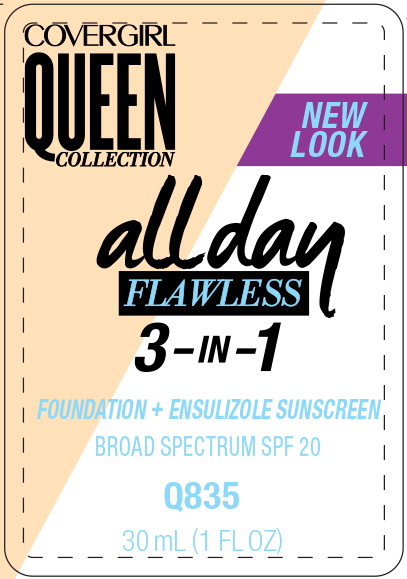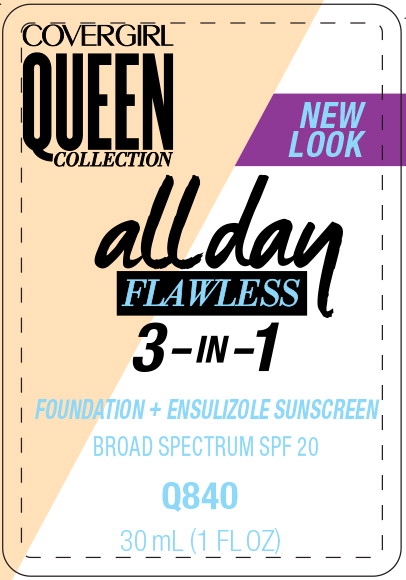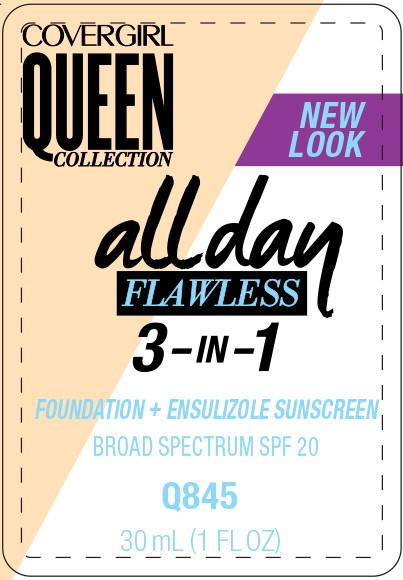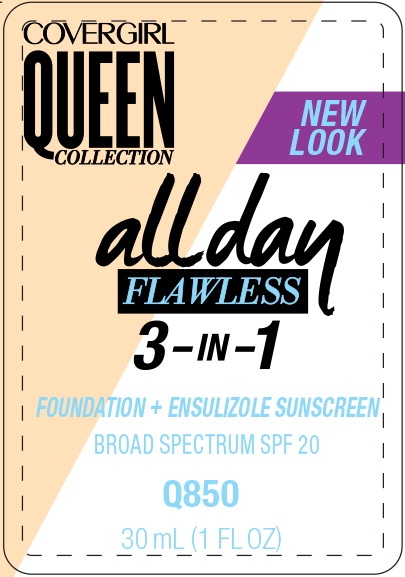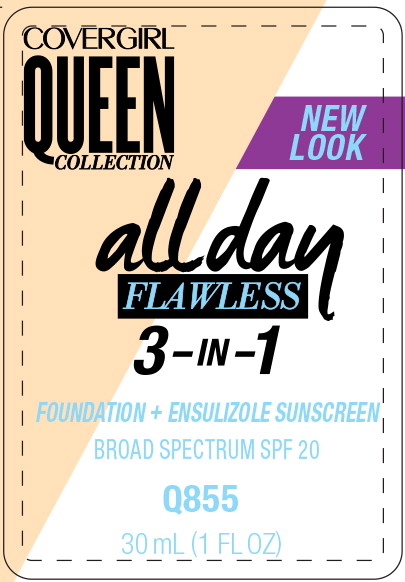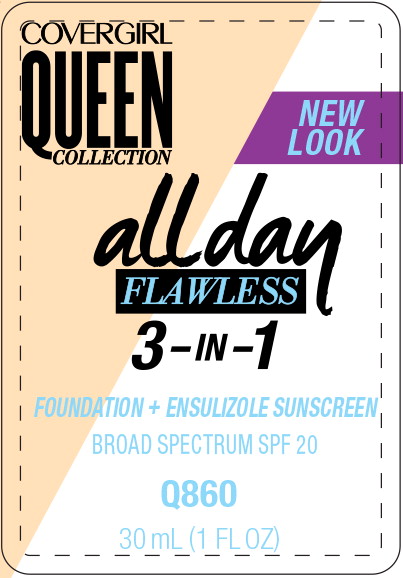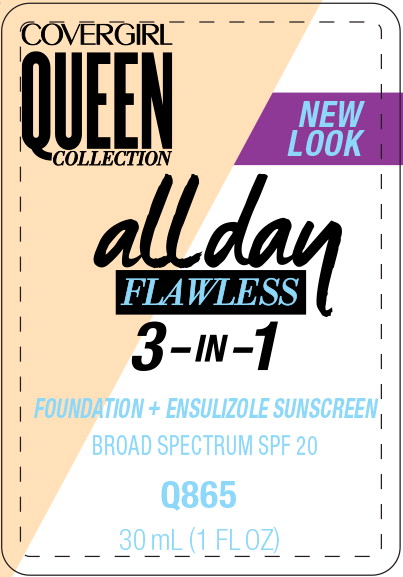 DRUG LABEL: Covergirl Queen Collection All Day Flawless 3in1 Foundation

NDC: 22700-141 | Form: LIQUID
Manufacturer: Noxell
Category: otc | Type: HUMAN OTC DRUG LABEL
Date: 20230124

ACTIVE INGREDIENTS: ENSULIZOLE 0.03 mg/1 mL
INACTIVE INGREDIENTS: WATER; CYCLOMETHICONE 5; PROPYLENE GLYCOL; TALC; DIMETHICONE; ALUMINUM STARCH OCTENYLSUCCINATE; SODIUM CHLORIDE; PEG/PPG-18/18 DIMETHICONE; BENZYL ALCOHOL; PHENOXYETHANOL; SODIUM HYDROXIDE; TRIHYDROXYSTEARIN; ARACHIDYL BEHENATE; SILICON DIOXIDE; SODIUM BENZOATE; HEXYL LAURATE; POLYGLYCERYL-4 ISOSTEARATE; ISOPROPYL TITANIUM TRIISOSTEARATE; ETHYLENE BRASSYLATE; BEHENIC ACID; HIGH DENSITY POLYETHYLENE; TITANIUM DIOXIDE

Drug Facts

Active ingredient

Ensulizole 3%

Purpose

Sunscreen

Uses

- helps prevent sunburn
- if used as directed with other sun protection measures (see Directions), decreases the risk of skin cancer and early skin aging caused by the sun

Warnings

- For external use only

- Do not use on damaged or broken skin

- When using this product keep out of eyes. Rinse with water to remove

- Stop use and ask a doctor if rash occurs

- Keep out of reach of children.

If product is swallowed, get medical help or contact a Poison Control Center right away

Directions

- apply liberally 15 minutes before sun exposure
- reapply at least every 2 hours
- use water resistant sunscreen if swimming or sweating
- Sun Protection Measures:

Spending time in the sun increases your risk of skin cancer and early skin aging. To decrease this risk, regularly use a sunscreen with a Broad Spectrum SPF value of 15 or higher and other sun protection measures including:

- limit time in sun, especially from 10 a.m. – 2 p.m.
- wear long-sleeved shirts, pants, hats, and sunglasses
- children under 6 months: ask a doctor

Other information

- protect this product from excessive heat and direct sun

Inactive ingredients

Water, cyclopentasiloxane, talc, propylene glycol, dimethicone, aluminum starch octenylsuccinate, sodium chloride, peg/ppg-18/18 dimethicone, pvp, benzyl alcohol, phenoxyethanol, sodium hydroxide, acrylonitrile/methyl methacrylate/vinylidene chloride copolymer, trihydroxystearin, methicone, arachidyl behenate, silica, sodium benzoate, synthetic wax, polyglyceryl-4 isostearate, hexyl laurate, cetyl peg/ppg-10/1 dimethicone, isopropyl titanium triisostearate, ethylene brassylate, behenic acid, polyethylene, iron oxides, titanium dioxide

Questions?

Call 1-800-426-8374

Principal Display Panel - Covergirl Queen Collection All Day 800 Label

COVERGIRL
QUEEN
COLLECTION

NEW LOOK

all day
FLAWLESS
3-IN-1

FOUNDATION + ENSULIZOLE SUNSCREEN

BROAD SPECTRUM SPF 20

Q800

30 mL (1 FL OZ)

Principal Display Panel - Covergirl Queen Collection All Day 805 Label

COVERGIRL
QUEEN
COLLECTION

NEW LOOK

all day
FLAWLESS
3-IN-1

FOUNDATION + ENSULIZOLE SUNSCREEN

BROAD SPECTRUM SPF 20

Q805

30 mL (1 FL OZ)

Principal Display Panel - Covergirl Queen Collection All Day 810 Label

COVERGIRL
QUEEN
COLLECTION

NEW LOOK

all day
FLAWLESS
3-IN-1

FOUNDATION + ENSULIZOLE SUNSCREEN

BROAD SPECTRUM SPF 20

Q810

30 mL (1 FL OZ)

Principal Display Panel - Covergirl Queen Collection All Day 815 Label

COVERGIRL
QUEEN
COLLECTION

NEW LOOK

all day
FLAWLESS
3-IN-1

FOUNDATION + ENSULIZOLE SUNSCREEN

BROAD SPECTRUM SPF 20

Q815

30 mL (1 FL OZ)

Principal Display Panel - Covergirl Queen Collection All Day 820 Label

COVERGIRL
QUEEN
COLLECTION

NEW LOOK

all day
FLAWLESS
3-IN-1

FOUNDATION + ENSULIZOLE SUNSCREEN

BROAD SPECTRUM SPF 20

Q820

30 mL (1 FL OZ)

Principal Display Panel - Covergirl Queen Collection All Day 825 Label

COVERGIRL
QUEEN
COLLECTION

NEW LOOK

all day
FLAWLESS
3-IN-1

FOUNDATION + ENSULIZOLE SUNSCREEN

BROAD SPECTRUM SPF 20

Q825

30 mL (1 FL OZ)

Principal Display Panel - Covergirl Queen Collection All Day 830 Label

COVERGIRL
QUEEN
COLLECTION

NEW LOOK

all day
FLAWLESS
3-IN-1

FOUNDATION + ENSULIZOLE SUNSCREEN

BROAD SPECTRUM SPF 20

Q830

30 mL (1 FL OZ)

Principal Display Panel - Covergirl Queen Collection All Day 835 Label

COVERGIRL
QUEEN
COLLECTION

NEW LOOK

all day
FLAWLESS
3-IN-1

FOUNDATION + ENSULIZOLE SUNSCREEN

BROAD SPECTRUM SPF 20

Q835

30 mL (1 FL OZ)

Principal Display Panel - Covergirl Queen Collection All Day 840 Label

COVERGIRL
QUEEN
COLLECTION

NEW LOOK

all day
FLAWLESS
3-IN-1

FOUNDATION + ENSULIZOLE SUNSCREEN

BROAD SPECTRUM SPF 20

Q840

30 mL (1 FL OZ)

Principal Display Panel - Covergirl Queen Collection All Day 845 Label

COVERGIRL
QUEEN
COLLECTION

NEW LOOK

all day
FLAWLESS
3-IN-1

FOUNDATION + ENSULIZOLE SUNSCREEN

BROAD SPECTRUM SPF 20

Q845

30 mL (1 FL OZ)

Principal Display Panel - Covergirl Queen Collection All Day 850 Label

COVERGIRL
QUEEN
COLLECTION

NEW LOOK

all day
FLAWLESS
3-IN-1

FOUNDATION + ENSULIZOLE SUNSCREEN

BROAD SPECTRUM SPF 20

Q850

30 mL (1 FL OZ)

Principal Display Panel - Covergirl Queen Collection All Day 855 Label

COVERGIRL
QUEEN
COLLECTION

NEW LOOK

all day
FLAWLESS
3-IN-1

FOUNDATION + ENSULIZOLE SUNSCREEN

BROAD SPECTRUM SPF 20

Q855

30 mL (1 FL OZ)

Principal Display Panel - Covergirl Queen Collection All Day 860 Label

COVERGIRL
QUEEN
COLLECTION

NEW LOOK

all day
FLAWLESS
3-IN-1

FOUNDATION + ENSULIZOLE SUNSCREEN

BROAD SPECTRUM SPF 20

Q860

30 mL (1 FL OZ)

Principal Display Panel - Covergirl Queen Collection All Day 865 Label

COVERGIRL
QUEEN
COLLECTION

NEW LOOK

all day
FLAWLESS
3-IN-1

FOUNDATION + ENSULIZOLE SUNSCREEN

BROAD SPECTRUM SPF 20

Q865

30 mL (1 FL OZ)